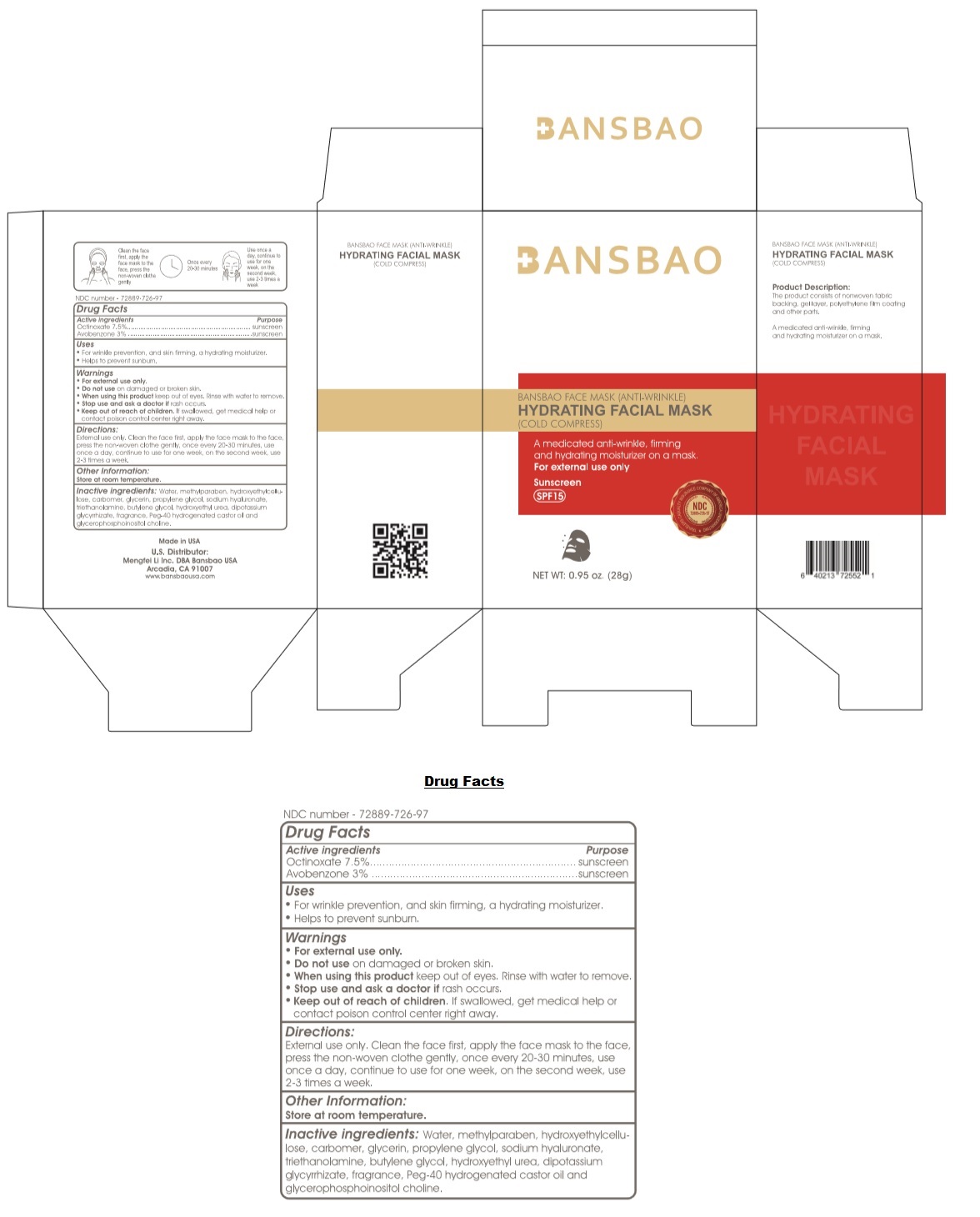 DRUG LABEL:  BANSBAO FACE MASK (ANTI-WRINKLE)
NDC: 72889-726 | Form: PATCH
Manufacturer: Mengfei Li  Inc.
Category: otc | Type: HUMAN OTC DRUG LABEL
Date: 20190403

ACTIVE INGREDIENTS: OCTINOXATE 7.5 g/100 mL; AVOBENZONE 3 g/100 mL
INACTIVE INGREDIENTS: WATER; METHYLPARABEN; HYDROXYETHYL ETHYLCELLULOSE; CARBOXYPOLYMETHYLENE; GLYCERIN; PROPYLENE GLYCOL; HYALURONATE SODIUM; TROLAMINE; BUTYLENE GLYCOL; HYDROXYETHYL UREA; GLYCYRRHIZINATE DIPOTASSIUM; FAGRAEA BERTEROANA FLOWER; POLYOXYL 40 HYDROGENATED CASTOR OIL; GLYCEROPHOSPHOINOSITOL CHOLINE

BANSBAO FACE MASK (ANTI-WRINKLE)

Active ingredients

Octinoxate 7.5 %

Avobenzone 3%

Purpose

sunscreen

Uses

- For wrinkle prevention, and skin firming, a hydrating moisturizer.
- Helps to prevent sunburn.

Warnings

- For external use only.
- Do not use on damaged or broken skin.
- When using this product keep out of eyes. Rinse with water to remove.
- Stop use and ask a doctor if rash occurs.

- Keep out of reach of children. If swallowed, get medical help or contact poison control center right away.

Directions:

External use only. Clean the face first, apply the face mask to the face, press the non-woven clothe gently, once every 20-30 minutes, use once a day, continue to use for one week, on the second week, use 2-3 times a week.

Other Information:

Store at room temperature.

Inactive ingredients:

Water, methylparaben, hydroxyethylcellulose, carbomer, glycerin, propylene glycol, sodium hyaluronate, triethanolamine, butylene glycol, hydroxyethyl urea, dipotassium glycyrrhizate, fragrance, Peg-40 hydrogenated castor oil and glycerophosphoinositol choline.

(COLD COMPRESS)

A medicated anti-wrinkle, firming and hydrating moisturizer on a mask.

Sunscreen

SPF 15

Product Description:

The product consists of nonwoven fabric backing, gel layer, polyethylene film coating and other parts.

Made in USA

U.S. Distributor:
Mengfei Li Inc. DBA Bansbao USA
Arcadia, CA 91007
www.bansbaousa.com